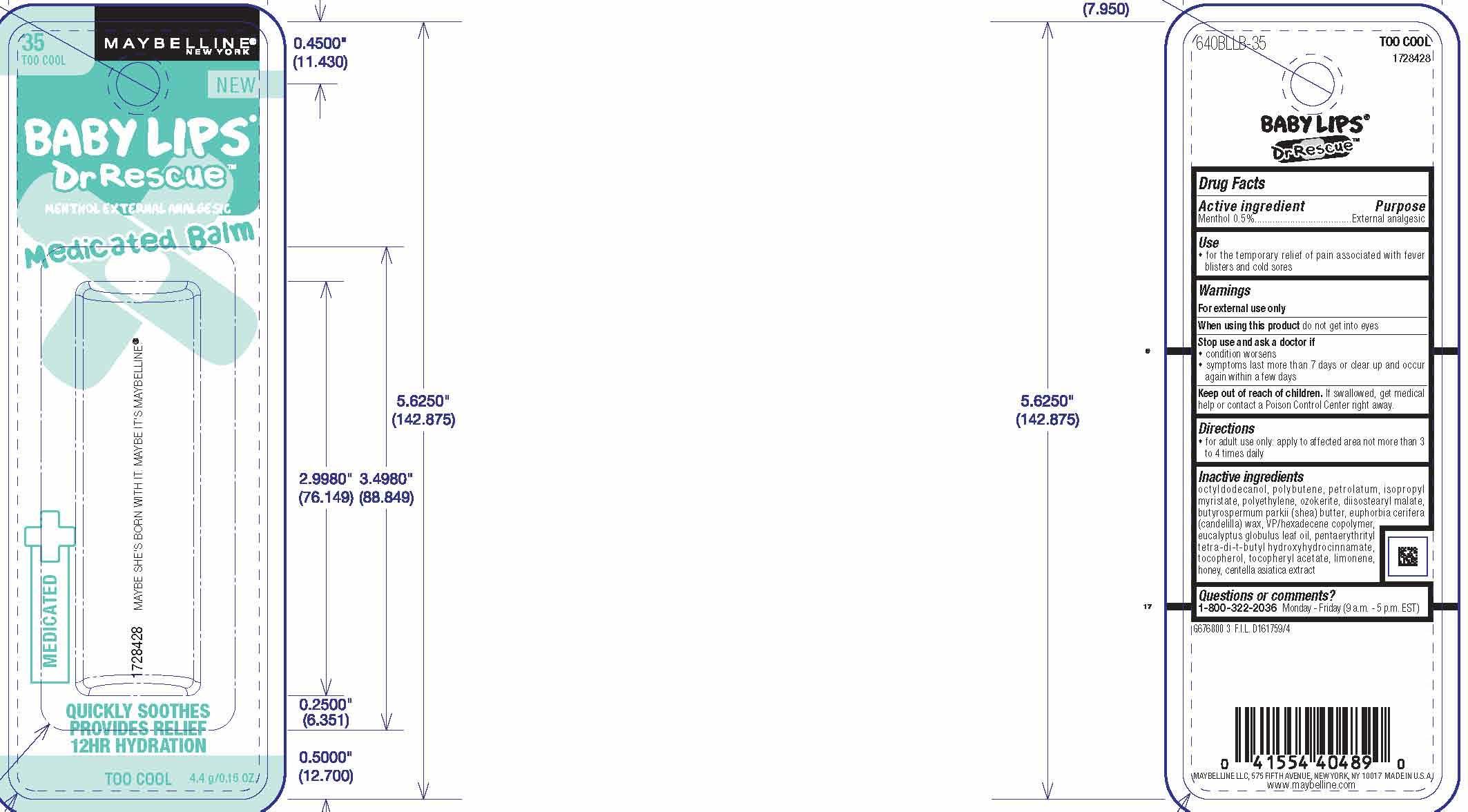 DRUG LABEL: Maybelline New York Baby Lips Dr Rescue Medicated Balm
NDC: 49967-489 | Form: LIPSTICK
Manufacturer: L'Oreal USA Products Inc
Category: otc | Type: HUMAN OTC DRUG LABEL
Date: 20231228

ACTIVE INGREDIENTS: MENTHOL 5 mg/1 g
INACTIVE INGREDIENTS: PETROLATUM; SHEA BUTTER; TOCOPHEROL

Drug Facts

Active Ingredient

Menthol 0.5%

Purpose

External analgesic

Use

for the temporary relief of pain associated with fever blisters and cold sores

Warnings

For external use only

When using this product

do not get into eyes

Stop use and ask a doctor if

condition worsens

symptoms last more than 7 days or clear up and occur again within a few days

Keep out of reach of children.

If swallowed, get medical help or contact a Poison Control Center right away.

Directions

for adult use only: apply to affected area not more than 3 to 4 times daily

Inactive ingredients

octyldodecanol, polybutene, petrolatum, isopropyl myristate, polyethylene, ozokerite, diisostearyl malate, butyrospermum parkii (shea) butter, euphorbia cerifera (candelilla) wax, VP/hexadecene copolymer, eucalyptus globulus leaf oil, penaerythrityl tetra-di-t-butyl hydroxyhydrocinamate, tocopherol, tocopheryl acetate, limonene, honey, centella asiatica extract

Questions or comments?

1-800-322-2036 Monday - Friday (9 a.m. - 5 p.m. EST)